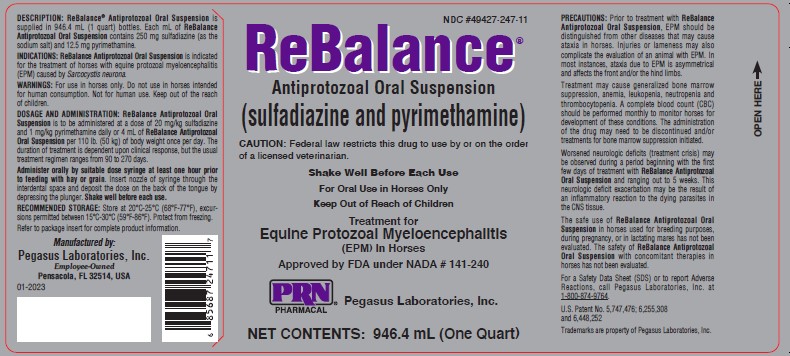 DRUG LABEL: ReBalance Antiprotozoal
NDC: 49427-247 | Form: SUSPENSION
Manufacturer: Pegasus Laboratories, Inc
Category: animal | Type: PRESCRIPTION ANIMAL DRUG LABEL
Date: 20231221

ACTIVE INGREDIENTS: SULFADIAZINE SODIUM 250 mg/1 mL; Pyrimethamine 12.5 mg/1 mL

ReBalance Antiprotozoal Oral Suspension

Approved by FDA under NADA # 141-240

ReBalance® Antiprotozoal Oral Suspension (sulfadiazine and pyrimethamine)

CAUTION:

Federal law restricts this drug to use by or on the order of a licensed veterinarian.

DESCRIPTION:

ReBalance Antiprotozoal Oral Suspension is supplied in 946.4 mL (1 quart) bottles. Each mL of ReBalance Antiprotozoal Oral Suspension contains 250 mg sulfadiazine (as the sodium salt) and 12.5 mg of pyrimethamine.

INDICATIONS:

ReBalance Antiprotozoal Oral Suspension is indicated for the treatment of horses with equine protozoal myeloencephalitis (EPM) caused by Sarcocystis neurona.

DOSAGE AND ADMINISTRATION:

ReBalance Antiprotozoal Oral Suspension is to be administered at a dose of 20 mg/kg sulfadiazine and 1 mg/kg pyrimethamine daily or 4 mL of ReBalance Antiprotozoal Oral Suspension per 110 lb. (50 kg) of body weight once per day. The duration of treatment is dependent upon clinical response, but the usual treatment regimen ranges from 90 to 270 days.

Administer orally by suitable dosing syringe at least one hour prior to feeding with hay or grain. Insert nozzle of syringe through the interdental space and deposit the dose on the back of the tongue by depressing the plunger. Shake well before use.

CONTRAINDICATIONS:

The use of ReBalance Antiprotozoal Oral Suspension in contraindicated in horses with known hypersensitivity to sulfonamide drugs or pyrimethamine.

WARNINGS:

For use in horses only. Do not use in horses intended for human consumption. Not for human use. Keep out of the reach of children.

PRECAUTIONS:

Prior to treatment with ReBalance Antiprotozoal Oral Suspension, EPM should be distinguished from the diseases that may cause ataxia in horses. injuries or lameness may also complicate the evaluation of an animal with EPM. In most instances, ataxia due to EPM is asymmetrical and affects the front and/or the hind limbs.

Treatment may cause generalized bone marrow suppression, anemia, leukopenia, neutropenia and thrombocytopenia. A complete blood count (CBC) should be performed monthly to monitor horses for development of these conditions. The administration of the drug may need to be discontinued and/or treatments for bone marrow suppression initiated.

Worsened neurologic deficits (treatment crisis) may be observed during a period beginning with the first few days of treatment with ReBalance Antiprotozoal Oral Suspension and ranging out to 5 weeks. This neurologic deficit exacerbation may be the result of an inflammatory reaction to the dying parasites in the CNS tissue.

The safe use of ReBalance Antiprotozoal Oral Suspension in horses used for breeding purposes during pregnancy, or in lactating mares has not been evaluated. The safety of ReBalance Antiprotozoal Oral Suspension with concomitant therapies in horses has not been evaluated.

ADVERSE REACTIONS:

Seventy-five horses (37 horses in the 1X group, 38 horses in the 2X group) that were treated with test article for at least 90 days were evaluated for adverse reaction.

Bone marrow suppression: Anemia: ReBalance Antiprotozoal Oral Suspension administration caused overall anemia (classification of anemia based on HBC, Hgb, and PCV/HCT values in 12% of the observations in the 1X group and 21% of the 2X group. In the 1X group, anemia was noted in in 22%, leukopenia in 19%, neutropenia in 5% and thrombocytopenia in 3% of the cases. In the 2X group, anemia was noted in 58%, leukopenia in 55%, neutropenia in 29% and thrombocytopenia in 5% of the cases. The incidence of bone marrow suppression in the 2X treatment group was two or more times that of the 1X group and the degree of suppression was more serious (mild to severe vs. mild to moderate). because of these blood dyscrasias, test article was interrupted over four times more often in horses treated at the 2X dosage than those treated 1X, Although both groups were off treatment for about the same amount of time (approximately 20% of the treatment period). In some instances of bone marrow suppression, diet was supplemented with folinic acid.

GI: Anorexia was observed in two horses in the 1X group and one hose in the 2X group. One horse in the 1X group and one horse in the 2X group were observed to be off feed. Observation of Anorexia and decreased appetite occurred predominately during the first 90 days of the treatment period. Observation of anorexia/decreased appetite in two of the above-referenced cases were due to unrelated illnesses. Loose stools were observed in three horses in the 1X group and five in the 2X group. The majority of these observations occurred in the first thirty days of treatment .

Diarrhea was observed in one horse in the 2X group on Day 4 of the study. The appearance of loose stool/diarrhea observations were self-limiting and resolved without treatment or discontinuation of test article. Brief, mild colic was observed in the three cases (one in the 1X group and two in the 2X group). colic was treated conservatively or not at all and resolved without sequelae.

Integument: Urticaria was observed in one horse in the 1X group and two horses in the 2X group. One horse was treated topically, two were untreated. All cases resolved without sequelae.

Treatment crisis: (marked worsening of the neurological condition) was reported in one horse in the 1X treatment group.

Depression/lethargy was observed infrequently occurred during the early part of the study in both groups and was primarily associated with the EPM syndrome. In one case, depression was associated with acute onset of a liver disorder.

Seizure: One horse in the 1X treatment group suffered from seizures. Seizure activity may be associated CNS damage from EPM.

CLINICAL PHARMACOLOGY:

Sulfonamides (a specific group of antimicrobial agents) and pyrimethamine are two different antimicrobial agents which inhibit folic acid synthesis at two different sites, in the same synthetic pathway. The combination of a sulfonamide and pyrimethamine is synergistic with the drug combination having an antiprotozoal effect.

EFFECTIVENESS SUMMARY:

A field effectiveness study was conducted at eight sites with eight investigators across the the United States. The study was conducted using historical controls. In the study each animal's response to treatment was compared to its pre-treatment values. The following standardized overall neurological dysfunction (OND) scale was used to grade the horses:

0 = Clinically normal. No detectable dysfunction.

1 = Slightly deficit. Dysfunction barely perceptible.

2 = Moderate deficit. Dysfunction easily detectable.

3 = Marked deficit. Dysfunction strikingly conspicuous.

4 = Severe deficit. profound dysfunction.5 = Recumbent.

ninety-seven horses were randomly assigned one of two treatment groups and administered a daily oral dose of ReBalance Antiprotozoal Oral Suspension for a minimum of 90 days. The two treatment groups were as follows:

(1) 1X labeled dose, 20 mg/kg sulfadiazine and 1 mg/kg pyrimethamine (48 horses); or

(2) 2X dose, twice the labeled dose, 40 mg/kg sulfadiazine and 2 mg/kg pyrimethamine (40 horses).

A physical examination and neurological evaluation and complete blood profile were conducted at the end of each 30-day treatment period for the first 90 days of treatment.

At the end of the 90-day treatment period, a videotape recording of the neurological condition and CSF and serum sample immunoblot and protein electrophoresis analysis were made. Based on the degree of clinical improvement and results of the CSF immunoblot analysis on test day 90 treatment in 30 day increments up to a period of 180 days was continued. In fourteen cases, the treatment was extended beyond 180 days (up to 270 days). A 30 day follow-up evaluation was made following cessation of treatment.

Treatment success was defined as: (1) horse that became CSF Western Blot Test negative with or without clinical improvement; and (2) a horse that remained CSF Western Blot Positive but demonstrated marked clinical improvement (two or more grade improvement from baseline OND score).

Only the 1X dose was evaluated for effectiveness due to the toxicity (bone marrow suppression) seen in the 2X dose. of the forty eight horses assigned to the 1X group, 26 horses completed the study. Based on the improvement in the OND scores and/or a negative CSF immunoblot, 16 out of the 26 horses (61.5%) were considered successes. Five of the 26 horses (19.2%) , had a negative CSF immunoblot by day 150 of the study. Three of these five horses were also clinically successes based on the improvement in OND scores. Fourteen of the 26 horses (53.8%) were corroborated as successes by masked expert evaluation and videotapes.

ANIMAL SAFETY:

ReBalance Antiprotozoal Oral Suspension was administered to ten horses (5 males and 5 females) ata dosage of 8 mL/50kg (110 lbs) a day (2X the labeled dose) for 92 days. Four horses (2 males and 2 females) were untreated controls.

Complete physical examinations, CBCs and serum chemistry values were determined on test days (TD) minus 14, TD minus 7, TD 0, biweekly throughout the 92 day treatment period and 14 and 29 days following the end of treatment.

Declines in RBC, HCT, Hgb and PCV were greater in the treated group and reached statistical significance. Twenty-nine days after cessation of treatment, blood parameter values returned to baseline levels. No clinical signals of anemia were observed in either group.

Most serum chemistry values remained within normal limits throughout the study in both groups. Alkaline phosphatase (ALP) values were evaluated (slightly above the upper end of the normal range) in three treated horses on study day 84 and 105.

Loose stool, along with infrequent diarrhea, were noted in the treatment group. The conditions were transient and required no medical intervention.

A depressed appetite of 1 to 2 days duration occurred infrequently in all but one of the treated horses. One horse became anorexic and required a change in diet.

ReBalance Antiprotozoal Oral Suspension administered at 2X the recommended label for 92 days resulted in clinical signs of toxicity including transient anemia and loose stools; however, medical intervention was not necessary,

STORAGE:

Store at 20°C-25°C (68°F-77°F), excursions permitted between 15°C-30°C (59°F-86°F). Protect from freezing.

HOW SUPPLIED:

Each mL of ReBalance Antiprotozoal Oral Suspension contains 250 mg of sulfadiazine (as the sodium salt) and 12.5 mg pyrimethamine and is available in 946.4 mL (1 Quart) multiple dose child resistant, screw-capped bottles.

GENERAL INFORMATION:

For a Safety Data Sheet (SDS) or to report Adverse Reactions, call Pegasus Laboratories, Inc. at 1-800-874-9764.

Manufactured by:

Pegasus Laboratories, Inc.

Employee Owned

Pensacola, FL 32514, USA

01-2023

PRINCIPAL DISPLAY PANEL:

NDC #49427-247-11

ReBalance

Antiprotozoal Oral Suspension

(sulfadiazine and pyrimethamine)

Caution: Federal law restricts this drug to use by or on the order of a licensed veterinarian.

Shake Well before Each Use

For oral Use in Horses Only

Keep Out of Reach of Children

Treatment for Equine Protozoal Myeloencephalitis (EPM) In Horses

Approved by FDA under NADA # 141-240

PRN Pharmacal, Pegasus Laboratories, Inc.

NET CONTENTS: 946.4 mL (One Quart)

Add image transcription here...